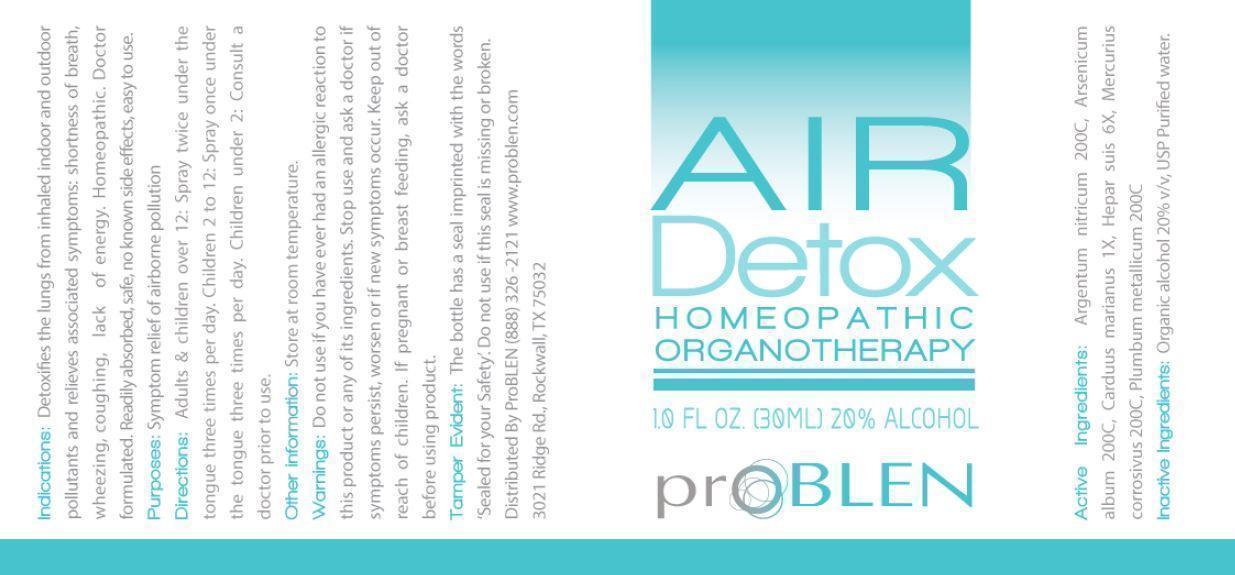 DRUG LABEL: Air Detox
NDC: 43853-0015 | Form: SPRAY
Manufacturer: Problen Pharmacy
Category: homeopathic | Type: HUMAN OTC DRUG LABEL
Date: 20150623

ACTIVE INGREDIENTS: SILVER NITRATE 200 [hp_C]/28 g; ARSENIC TRIOXIDE 200 [hp_C]/28 g; MILK THISTLE 1 [hp_X]/28 g; PORK LIVER 6 [hp_X]/28 g; MERCURIC CHLORIDE 200 [hp_C]/28 g; LEAD 200 [hp_C]/28 g
INACTIVE INGREDIENTS: ALCOHOL; WATER

ACTIVE INGREDIENT

Active Ingredients: argentum nitricum 200C, arsenicum album 200C, carduus marianus 1X, hepar suis 6X, mercurius corrosivus 200C, plumbum metallicum 200C

PURPOSE

Purposes: symptom relief of airborne pollution

Keep out of reach of children.

INDICATIONS AND USAGE

Indications: Detoxifies the lungs from inhaled indoor and outdoor pollutants and relieves associated symptoms: shortness of breath, wheezing, coughing, lack of energy. Homeopathic. Doctor formulated. Readily absorbed, safe, no known side effects, easy to use.

DOSAGE AND ADMINISTRATION

Directions: Adults & children over 12: spray twice under the tongue three times per day. Children 2 to 12: spray once under the tongue three times per day. Children under 2: consult a doctor prior to use.

WARNINGS

Warnings: Do not use if you have ever had an allergic reaction to this product or any of its ingredients. Stop use and ask a doctor if symptoms persist, worsen or if new symptoms occur. If pregnant or breast feeding, ask a doctor before using product.

Other information: Store at room temperature.

Tamper Evident: The bottle has a seal imprinted with the words "sealed for your safety." Do not use if this seal is missing or broken.

INACTIVE INGREDIENT

Inactive Ingredients: organic alcohol 20% v/v, USP purified water.